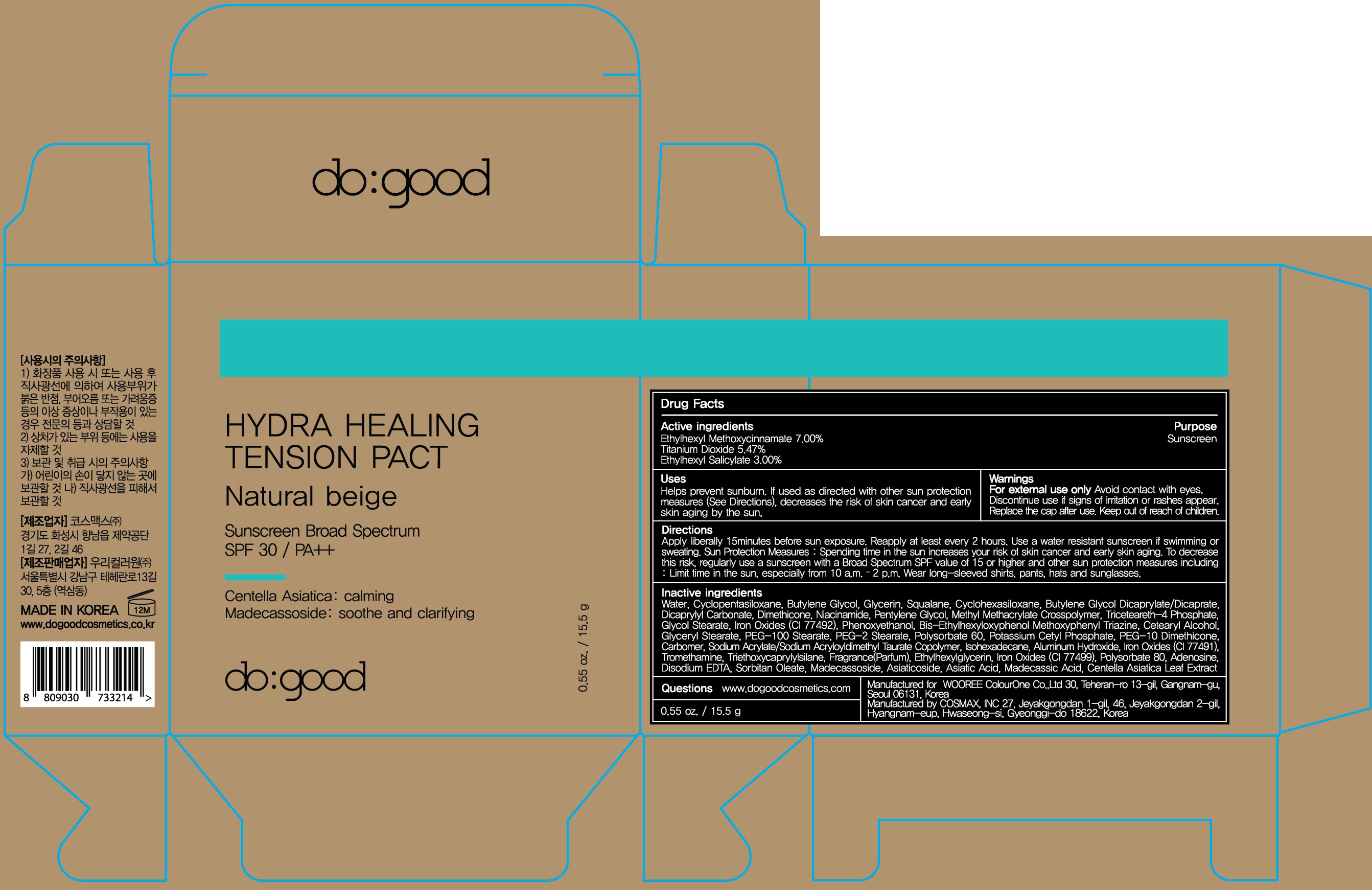 DRUG LABEL: do good Hydra Healing Tension Pact Natural Beige
NDC: 72058-090 | Form: POWDER
Manufacturer: WOOREE Colourone Co.,Ltd
Category: otc | Type: HUMAN OTC DRUG LABEL
Date: 20180313

ACTIVE INGREDIENTS: Octinoxate 1.08 g/15.5 g; Titanium Dioxide 0.84 g/15.5 g; Octisalate 0.46 g/15.5 g
INACTIVE INGREDIENTS: Water; Butylene Glycol

ACTIVE INGREDIENT

Active ingredients: Ethylhexyl Methoxycinnamate 7.00%, Titanium Dioxide 5.47%, Ethylhexyl Salicylate 3.00%

INACTIVE INGREDIENT

Inactive ingredients:

Water, Cyclopentasiloxane, Butylene Glycol, Glycerin, Squalane, Cyclohexasiloxane, Butylene Glycol Dicaprylate/Dicaprate, Dicaprylyl Carbonate, Dimethicone, Niacinamide, Pentylene Glycol, Methyl Methacrylate Crosspolymer, Triceteareth-4 Phosphate, Glycol Stearate, Iron Oxides (CI 77492), Phenoxyethanol, Bis-Ethylhexyloxyphenol Methoxyphenyl Triazine, Cetearyl Alcohol, Glyceryl Stearate, PEG-100 Stearate, PEG-2 Stearate, Polysorbate 60, Potassium Cetyl Phosphate, PEG-10 Dimethicone, Carbomer, Sodium Acrylate/Sodium Acryloyldimethyl Taurate Copolymer, Isohexadecane, Aluminum Hydroxide, Iron Oxides (CI 77491), Tromethamine, Triethoxycaprylylsilane, Fragrance(Parfum), Ethylhexylglycerin, Iron Oxides (CI 77499), Polysorbate 80, Adenosine, Disodium EDTA, Sorbitan Oleate, Madecassoside, Asiaticoside, Asiatic Acid, Madecassic Acid, Centella Asiatica Leaf Extract

PURPOSE

Purpose: Sunscreen

WARNINGS

For external use only.

Avoid contact with eyes.

Discontinue use if signs of irritation or rashes appear.

Replace the cap after use.

Keep out of reach of children

DESCRIPTION

Uses:

Helps prevent sunburn.

If used as directed with other sun protection measures (See Directions), decreases the risk of skin cancer and early skin aging by the sun.

Directions:

Apply liberally 15 minutes before sun exposure

Reapply at least every 2 hours

Use a water resistant sunscreen if swimming or sweating

Sun Protection Measures: Spending time in the sun increases your risk of skin cancer and early skin aging.

To decrease this risk, regularly use a sunscreen with a Broad Spectrum SPF value of 15 or higher and other sun protection measures including:

Limit time in the sun, especially from 10 a.m. – 2 p.m.

Wear long-sleeved shirts, pants, hats and sunglasses